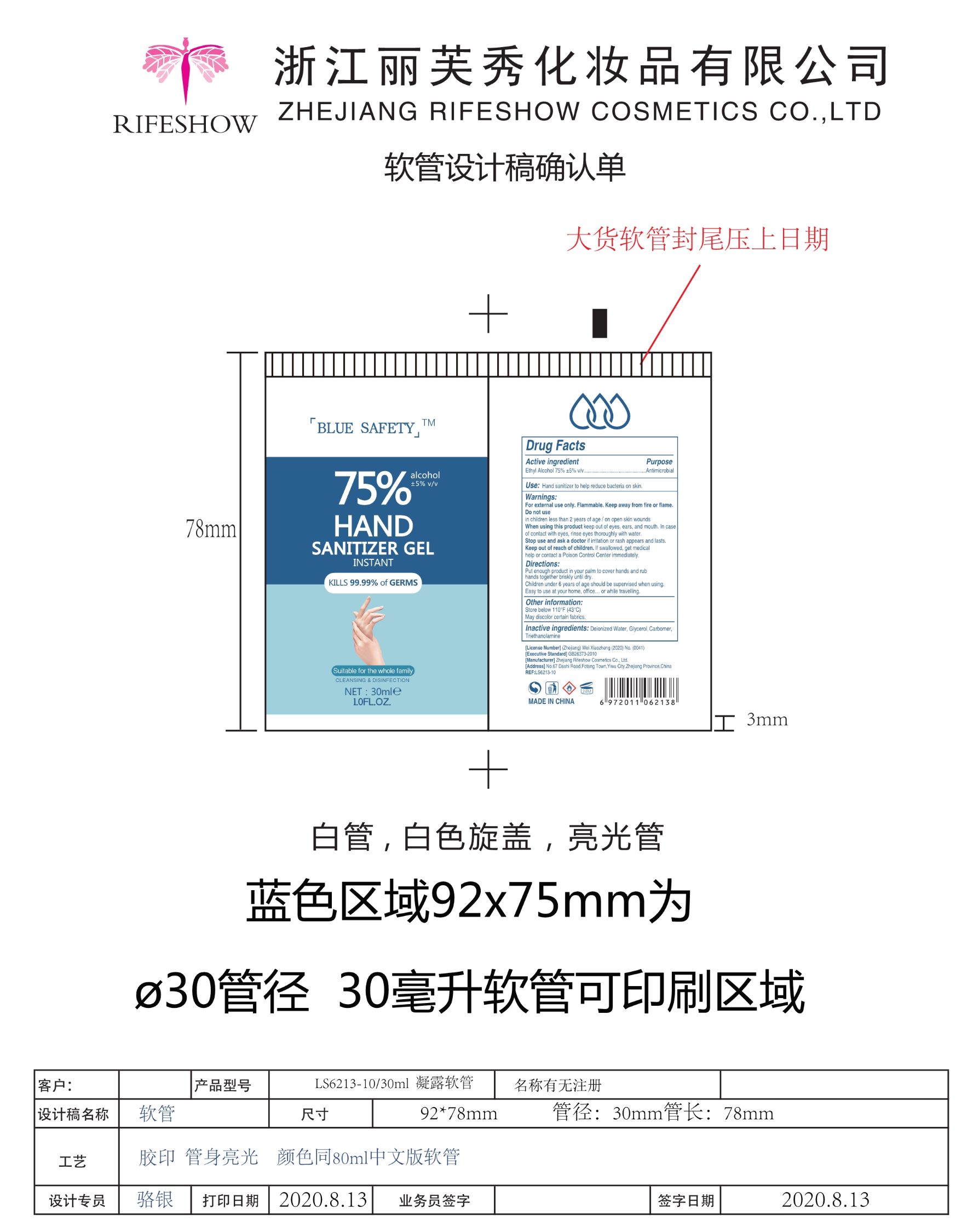 DRUG LABEL: HAND SANITIZER
NDC: 56084-027 | Form: GEL
Manufacturer: Zhejiang RIFESHOW Cosmetics Co., Ltd.
Category: otc | Type: HUMAN OTC DRUG LABEL
Date: 20200828

ACTIVE INGREDIENTS: ALCOHOL 75 mL/100 mL
INACTIVE INGREDIENTS: WATER; POLYACRYLIC ACID (250000 MW); GLYCERIN; TROLAMINE

Zhejiang RIFESHOW Cosmetics Co., Ltd.
HAND SANITIZER 30ml
56084-027-01

Active Ingredient(s)

Ethyl Alcohol 75%±5% v/v

Purpose

Antimicrobial

Use

Hand sanitizer to help reduce bacteria on skin.

Warnings

- For external use only.
- Flammable. Keep away from fire or flame.

Do not use

- on children less than 2 years of age.
- on open wounds/cuts.

When using this product keep out of eyes, ears, and mouth. In case of contact with eyes, rinse eyes thoroughly with water.

Stop use and ask a doctor if irritation or rash appears and lasts.

Keep out of reach of children. If swallowed, get medical help or contact a Poison Control center immediately.

Directions

Put enough product in your palm to cover hands and rub hands together briskly until dry.
Children under 6 years of age should be supervised when using. Easy to use at your home, office... or while travelling.

Other information

- Store below 110℉(43℃)
- May discolor certain fabrics.

Inactive ingredients

Deionized Water, Glycerol, Carbomer, Triethanolamine.

Package Label - Principal Display Panel

30 mL NDC: 56084-027-01